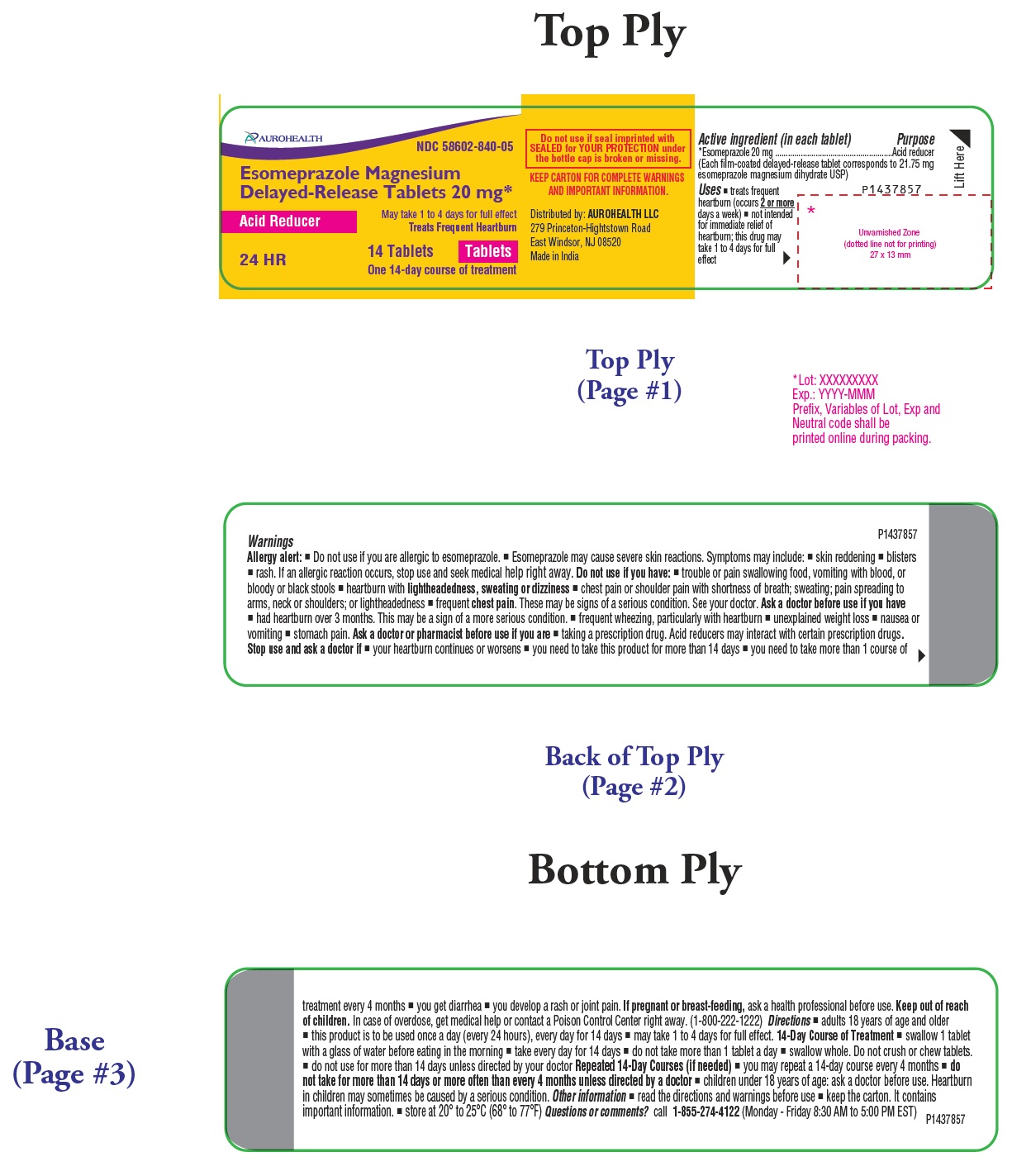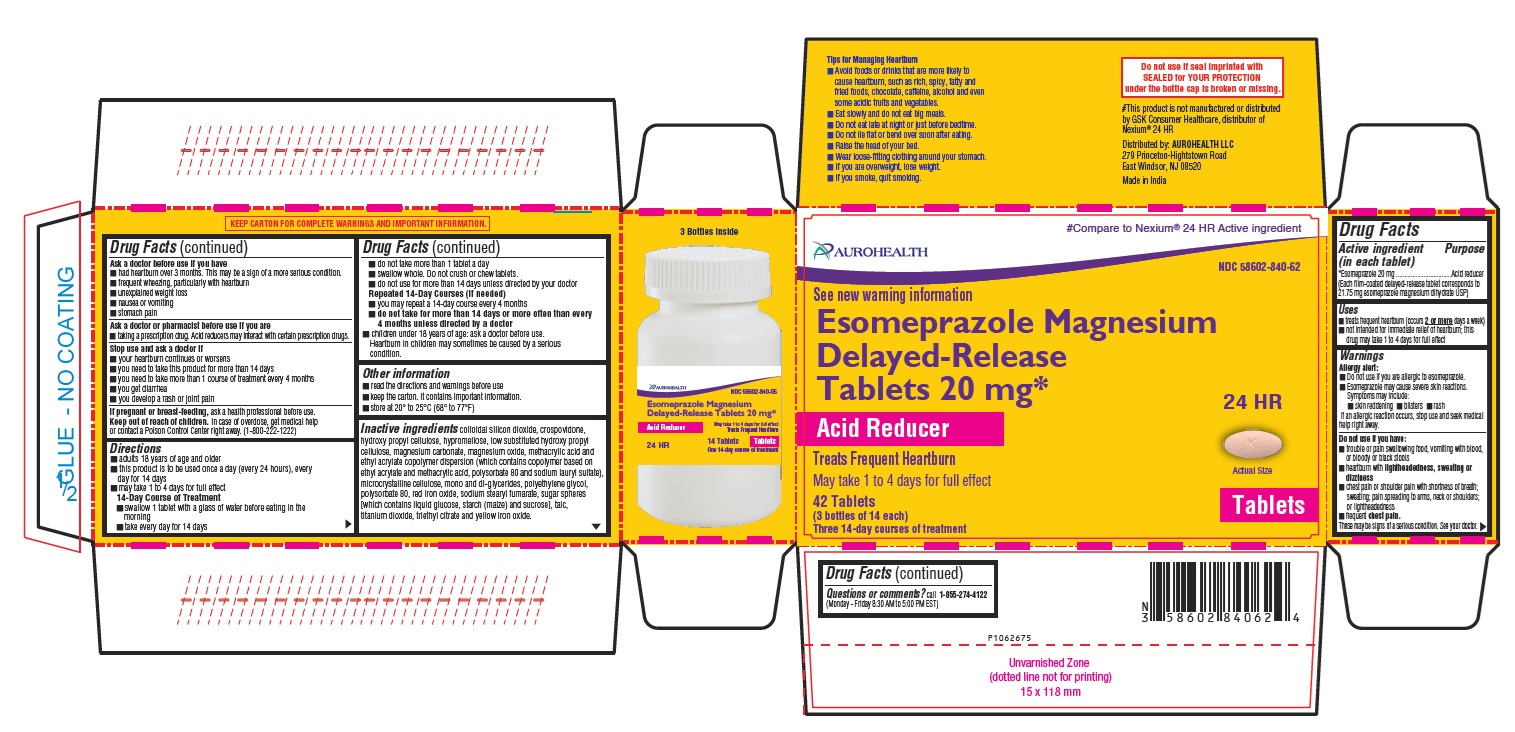 DRUG LABEL: Esomeprazole Magnesium
NDC: 58602-840 | Form: TABLET, DELAYED RELEASE
Manufacturer: Aurohealth LLC
Category: otc | Type: Human OTC Drug Label
Date: 20260212

ACTIVE INGREDIENTS: ESOMEPRAZOLE MAGNESIUM DIHYDRATE 20 mg/1 1
INACTIVE INGREDIENTS: SILICON DIOXIDE; CROSPOVIDONE (120 .MU.M); HYDROXYPROPYL CELLULOSE (20000 WAMW); HYPROMELLOSE 2910 (3 MPA.S); HYPROMELLOSE 2910 (6 MPA.S); LOW-SUBSTITUTED HYDROXYPROPYL CELLULOSE (11% HYDROXYPROPYL; 130000 MW); MAGNESIUM CARBONATE; MAGNESIUM OXIDE; METHACRYLIC ACID - ETHYL ACRYLATE COPOLYMER (1:1) TYPE A; POLYSORBATE 80; SODIUM LAURYL SULFATE; MICROCRYSTALLINE CELLULOSE 301; MICROCRYSTALLINE CELLULOSE 302; GLYCERYL MONO AND DIPALMITOSTEARATE; POLYETHYLENE GLYCOL 6000; FERRIC OXIDE RED; SODIUM STEARYL FUMARATE; DEXTROSE, UNSPECIFIED FORM; STARCH, CORN; SUCROSE; TALC; TITANIUM DIOXIDE; TRIETHYL CITRATE; FERRIC OXIDE YELLOW

Esomeprazole Magnesium Delayed-Release Tablets 20 mg*

Drug Facts

Active ingredient (in each tablet)

*Esomeprazole 20 mg
(Each film-coated delayed-release tablet corresponds to 21.75 mg esomeprazole magnesium dihydrate USP)

Purpose

Acid reducer

Uses

- treats frequent heartburn (occurs 2 or more days a week)
- not intended for immediate relief of heartburn; this drug may take 1 to 4 days for full effect

Warnings

Allergy alert:
■ Do not use if you are allergic to esomeprazole.
■ Esomeprazole may cause severe skin reactions.
Symptoms may include:
■ skin reddening ■ blisters ■ rash
If an allergic reaction occurs, stop use and seek medical help right away.

Do not use if you have:

- trouble or pain swallowing food, vomiting with blood, or bloody or black stools
- heartburn with lightheadedness, sweating or dizziness
- chest pain or shoulder pain with shortness of breath; sweating; pain spreading to arms, neck or shoulders; or lightheadedness
- frequent chest pain.

These may be signs of a serious condition. See your doctor.

Ask a doctor before use if you have

- had heartburn over 3 months. This may be a sign of a more serious condition.
- frequent wheezing, particularly with heartburn
- unexplained weight loss
- nausea or vomiting
- stomach pain

Ask a doctor or pharmacist before use if you are

- taking a prescription drug. Acid reducers may interact with certain prescription drugs.

Stop use and ask a doctor if

- your heartburn continues or worsens
- you need to take this product for more than 14 days
- you need to take more than 1 course of treatment every 4 months
- you get diarrhea
- you develop a rash or joint pain

If pregnant or breast-feeding, ask a health professional before use.

Keep out of reach of children. In case of overdose, get medical help or contact a Poison Control Center right away. (1-800-222-1222)

Directions

- adults 18 years of age and older
- this product is to be used once a day (every 24 hours), every day for 14 days
- may take 1 to 4 days for full effect

14-Day Course of Treatment

- swallow 1 tablet with a glass of water before eating in the morning
- take every day for 14 days
- do not take more than 1 tablet a day
- swallow whole. Do not crush or chew tablets.
- do not use for more than 14 days unless directed by your doctor

Repeated 14-Day Courses (if needed)

- you may repeat a 14-day course every 4 months
- do not take for more than 14 days or more often than every 4 months unless directed by a doctor
- children under 18 years of age: ask a doctor before use. Heartburn in children may sometimes be caused by a serious condition.

Other information

- read the directions and warnings before use
- keep the carton. It contains important information.
- store at 20° to 25°C (68° to 77°F)

Inactive ingredients

colloidal silicon dioxide, crospovidone, hydroxy propyl cellulose, hypromellose, low substituted hydroxy propyl cellulose, magnesium carbonate, magnesium oxide, methacrylic acid and ethyl acrylate copolymer dispersion (which contains copolymer based on ethyl acrylate and methacrylic acid, polysorbate 80 and sodium lauryl sulfate), microcrystalline cellulose, mono and di-glycerides, polyethylene glycol, polysorbate 80, red iron oxide, sodium stearyl fumarate, sugar spheres [which contains liquid glucose, starch (maize) and sucrose], talc, titanium dioxide, triethyl citrate and yellow iron oxide.

Questions or comments? call 1-855-274-4122 (Monday – Friday 8:30 AM to 5:00 PM EST)

Tips for Managing Heartburn

- Avoid foods or drinks that are more likely to cause heartburn, such as rich, spicy, fatty and fried foods, chocolate, caffeine, alcohol and even some acidic fruits and vegetables.
- Eat slowly and do not eat big meals.
- Do not eat late at night or just before bedtime.
- Do not lie flat or bend over soon after eating.
- Raise the head of your bed.
- Wear loose-fitting clothing around your stomach.
- If you are overweight, lose weight.
- If you smoke, quit smoking.

Distributed by:
AUROHEALTH LLC
279 Princeton-Hightstown Road
East Windsor, NJ 08520
Made in India

PACKAGE LABEL-PRINCIPAL DISPLAY PANEL - 20 mg (14 Tablets)

AUROHEALTH
NDC 58602-840-05
Esomeprazole Magnesium
Delayed-Release Tablets 20 mg*
Acid Reducer
24 HR
May take 1 to 4 days for full effect
Treats Frequent Heartburn
14 Tablets Tablets
One 14-day course of treatment

PACKAGE LABEL-PRINCIPAL DISPLAY PANEL - 20 mg (42 Tablets)

#Compare to Nexium® 24 HR Active ingredient
AUROHEALTH
NDC 58602-840-62
See new warning information
Esomeprazole Magnesium
Delayed-Release
Tablets 20 mg*
Acid Reducer
24 HR
Treats Frequent Heartburn
May take 1 to 4 days for full effect

Actual Size
Tablets
42 Tablets

(3 bottles of 14 each)
Three 14-day courses of treatment